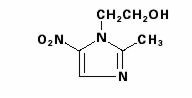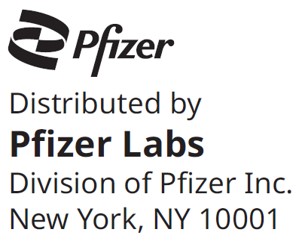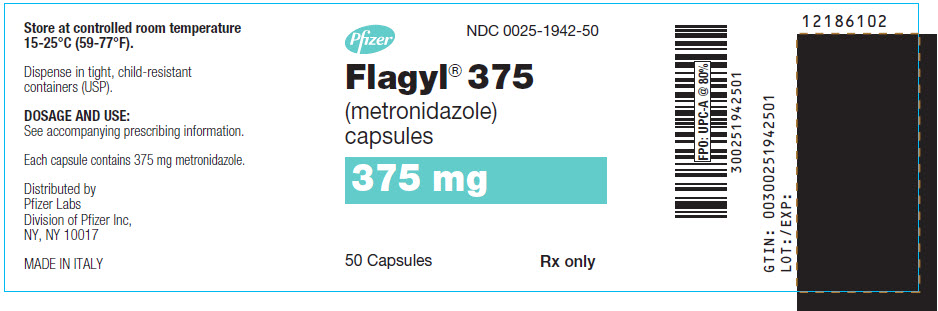 DRUG LABEL: Flagyl
NDC: 0025-1942 | Form: CAPSULE
Manufacturer: Pfizer Laboratories Div Pfizer Inc
Category: prescription | Type: HUMAN PRESCRIPTION DRUG LABEL
Date: 20250723

ACTIVE INGREDIENTS: METRONIDAZOLE 375 mg/1 1
INACTIVE INGREDIENTS: STARCH, CORN; MAGNESIUM STEARATE; GELATIN, UNSPECIFIED; FERROSOFERRIC OXIDE; TITANIUM DIOXIDE; FD&C GREEN NO. 3; D&C YELLOW NO. 10

FLAGYL®
(metronidazole) capsules

To reduce the development of drug-resistant bacteria and maintain the effectiveness of FLAGYL® and other antibacterial drugs, FLAGYL® should be used only to treat or prevent infections that are proven or strongly suspected to be caused by bacteria.

WARNING

Metronidazole has been shown to be carcinogenic in mice and rats (see PRECAUTIONS). Unnecessary use of the drug should be avoided. Its use should be reserved for the conditions described in the INDICATIONS AND USAGE section below.

DESCRIPTION

FLAGYL (metronidazole) capsules, 375 mg is an oral formulation of the synthetic nitroimidazole antimicrobial agent, 2-methyl-5-nitro-1H-imidazole-1-ethanol, which has the following structural formula:

FLAGYL (metronidazole) capsules, 375 mg, (indicated below as FLAGYL 375 capsules) contain 375 mg of metronidazole USP. Inactive ingredients include corn starch, magnesium stearate, gelatin, black iron oxide, titanium dioxide, FD&C Green No. 3, and D&C Yellow No. 10.

CLINICAL PHARMACOLOGY

Absorption

Disposition of metronidazole in the body is similar for both oral and intravenous dosage forms.

FLAGYL 375 capsules have been shown to have a rate and extent of absorption similar to metronidazole tablets (FLAGYL) and were bioequivalent at an equal single dose of 750 mg. In a study conducted with 23 adult, healthy, female volunteers, oral administration of two 375 mg FLAGYL capsules under fasted conditions produced a mean (±1 SD) peak plasma concentration (Cmax) of 21.4 (±2.8) mcg/mL with a mean Tmax of 1.6 (± 0.7) hours and a mean area under the plasma concentration-time curve (AUC) of 223 (±44) mcg∙hr/mL. In the same study, three 250 mg FLAGYL tablets produced a mean Cmax of 20.4 (± 3.8) mcg/mL with a mean Tmax of 1.4 (± 0.4) hours and a mean AUC of 218 (± 50) mcg∙hr/mL.

Administration of FLAGYL 375 capsules with food does not affect the extent of absorption of metronidazole; however, the presence of food results in a lower Cmax and a delayed Tmax compared to fasted conditions. In a study of 14 healthy, adult, female volunteers, administration of FLAGYL 375 capsules under fasting conditions produced a mean Cmax of 10.9 (± 1.5) mcg/mL, a mean Tmax of 1.5 (± 1.4) hours, and a mean AUC of 110 (± 34) mcg∙hr/mL compared to a mean Cmax of 8.6 (± 1.6) mcg/mL, a mean Tmax of 4.2 (± 1.7) hours, and a mean AUC of 99 (± 14) mcg∙hr/mL under fed conditions.

Distribution

Metronidazole is the major component appearing in the plasma, with lesser quantities of metabolites also being present. Less than 20% of the circulating metronidazole is bound to plasma proteins. Metronidazole appears in cerebrospinal fluid, saliva, and breast milk in concentrations similar to those found in plasma. Bactericidal concentrations of metronidazole have also been detected in pus from hepatic abscesses.

Metabolism/Excretion

The major route of elimination of metronidazole and its metabolites is via the urine (60% to 80% of the dose), with fecal excretion accounting for 6% to 15% of the dose. The metabolites that appear in the urine result primarily from side-chain oxidation [1-(ß-hydroxyethyl)-2-hydroxymethyl-5-nitroimidazole and 2-methyl-5-nitroimidazole-1-yl-acetic acid] and glucuronide conjugation, with unchanged metronidazole accounting for approximately 20% of the total. Both the parent compound and the hydroxyl metabolite possess in vitro antimicrobial activity against most strains of anaerobic bacteria and in vitro trichomonacidal activity.

Renal clearance of metronidazole is approximately 10 mL/min/1.73 m^2. The average elimination half-life of metronidazole in healthy subjects is eight hours.

Renal Impairment

Decreased renal function does not alter the single-dose pharmacokinetics of metronidazole.

Subjects with end-stage renal disease (ESRD; CLCR=8.1±9.1 mL/min) and who received a single intravenous infusion of metronidazole 500 mg had no significant change in metronidazole pharmacokinetics but had 2-fold higher Cmax of hydroxy-metronidazole and 5-fold higher Cmax of metronidazole acetate, compared to healthy subjects with normal renal function (CLCR=126±16 mL/min). Thus, on account of the potential accumulation of metronidazole metabolites in ESRD patients, monitoring for metronidazole associated adverse events is recommended (see PRECAUTIONS).

Effect of Dialysis

Following a single intravenous infusion or oral dose of metronidazole 500 mg, the clearance of metronidazole was investigated in ESRD subjects undergoing hemodialysis or continuous ambulatory peritoneal dialysis (CAPD). A hemodialysis session lasting for 4 to 8 hours removed 40% to 65% of the administered metronidazole dose, depending on the type of dialyzer membrane used and the duration of the dialysis session. If the administration of metronidazole cannot be separated from the dialysis session, supplementation of metronidazole dose following hemodialysis should be considered (see DOSAGE AND ADMINISTRATION). A peritoneal dialysis session lasting for 7.5 hours removed approximately 10% of the administered metronidazole dose. No adjustment in metronidazole dose is needed in ESRD patients undergoing CAPD.

Hepatic Impairment

Following a single intravenous infusion of 500 mg metronidazole, the mean AUC24 of metronidazole was higher by 114% in patients with severe (Child-Pugh C) hepatic impairment, and by 54% and 53% in patients with mild (Child-Pugh A) and moderate (Child-Pugh B) hepatic impairment, respectively, compared to healthy control subjects. There were no significant changes in the AUC24 of hydroxy-metronidazole in these hepatically impaired patients. Pharmacokinetic modeling and simulation indicates the metronidazole dosage in amebiasis should be reduced by 50% and the dosage interval for trichomoniasis should be increased from every 12 hours to every 24 hours in patients with severe (Child-Pugh C) hepatic impairment. No dosage adjustment is needed for patients with mild to moderate hepatic impairment. Patients with hepatic impairment should be monitored for metronidazole associated adverse events (see PRECAUTIONS and DOSAGE AND ADMINISTRATION).

Geriatric Patients

Following a single 500 mg oral or IV dose of metronidazole, subjects >70 years old with no apparent renal or hepatic dysfunction had a 40% to 80% higher mean AUC of hydroxy-metronidazole (active metabolite), with no apparent increase in the mean AUC of metronidazole (parent compound), compared to young healthy controls <40 years old. In geriatric patients, monitoring for metronidazole associated adverse events is recommended (see PRECAUTIONS).

Pediatric Patients

In one study, newborn infants appeared to demonstrate diminished capacity to eliminate metronidazole. The elimination half-life, measured during the first 3 days of life, was inversely related to gestational age. In infants whose gestational ages were between 28 and 40 weeks, the corresponding elimination half-lives ranged from 109 to 22.5 hours.

Microbiology

Mechanism of Action

Metronidazole, a nitroimidazole, exerts antibacterial effects in an anaerobic environment against most obligate anaerobes. Once metronidazole enters the organism by passive diffusion and activated in the cytoplasm of susceptible anaerobic bacteria, it is reduced; this process includes intra-cellular electron transport proteins such as ferredoxin, transfer of an electron to the nitro group of the metronidazole, and formation of a short-lived nitroso free radical. Because of this alteration of the metronidazole molecule, a concentration gradient is created and maintained which promotes the drug's intracellular transport. The reduced form of metronidazole and free radicals can interact with DNA leading to inhibition of DNA synthesis and DNA degradation leading to death of the bacteria. The precise mechanism of action of metronidazole is unclear.

Resistance

A potential for development of resistance exists against metronidazole.

Resistance may be due to multiple mechanisms that include decreased uptake of the drug, altered reduction efficiency, overexpression of the efflux pumps, inactivation of the drug, and/or increased DNA damage repair.

Metronidazole does not possess any clinically relevant activity against facultative anaerobes or obligate aerobes.

Antimicrobial activity

Metronidazole has been shown to be active against most isolates of the following bacteria both in vitro and in clinical infections as described in the INDICATIONS AND USAGE section.

Gram-positive anaerobes:
Clostridium species
Eubacterium species
Peptococcus species
Peptostreptococcus species

Gram-negative anaerobes:
Bacteroides fragilis group (B. fragilis, B. distasonis, B. ovatus, B. thetaiotaomicron, B.vulgatus)
Fusobacterium species

Protozoal parasites:
Entamoeba histolytica
Trichomonas vaginalis

The following in vitro data are available, but their clinical significance is unknown.

Metronidazole exhibits in vitro minimal inhibitory concentrations (MICs) of 8 mcg/mL or less against most (≥90%) isolates of the following bacteria; however, the safety and effectiveness of metronidazole in treating clinical infections due to these bacteria have not been established in adequate and well-controlled clinical trials.

Gram-negative anaerobes
Bacteroides fragilis group (B. caccae, B. uniformis)
Prevotella species (P. bivia, P. buccae, P. disiens)

Susceptibility Testing

For specific information regarding susceptibility test interpretive criteria and associated test methods and quality control standards recognized by FDA for this drug, please see: https://www.fda.gov/STIC.

INDICATIONS AND USAGE

Symptomatic Trichomoniasis. FLAGYL 375 capsules are indicated for the treatment of T. vaginalis infection in females and males when the presence of the trichomonad has been confirmed by appropriate laboratory procedures (wet smears and/or cultures).

Asymptomatic Trichomoniasis. FLAGYL 375 capsules are indicated in the treatment of asymptomatic T. vaginalis infection in females when the organism is associated with endocervicitis, cervicitis, or cervical erosion. Since there is evidence that presence of the trichomonad can interfere with accurate assessment of abnormal cytological smears, additional smears should be performed after eradication of the parasite.

Treatment of Asymptomatic Sexual Partners. T. vaginalis infection is a venereal disease. Therefore, asymptomatic sexual partners of treated patients should be treated simultaneously if the organism has been found to be present, in order to prevent reinfection of the partner. The decision as to whether to treat an asymptomatic male partner who has a negative culture or one for whom no culture has been attempted is an individual one. In making this decision, it should be noted that there is evidence that a woman may become reinfected if her sexual partner is not treated. Also, since there can be considerable difficulty in isolating the organism from the asymptomatic male carrier, negative smears and cultures cannot be relied upon in this regard. In any event, the sexual partner should be treated with metronidazole in cases of reinfection.

Amebiasis. FLAGYL 375 capsules are indicated in the treatment of acute intestinal amebiasis (amebic dysentery) and amebic liver abscess.

In amebic liver abscess, FLAGYL 375 capsules therapy does not obviate the need for aspiration or drainage of pus.

Anaerobic Bacterial Infections. FLAGYL 375 capsules are indicated in the treatment of serious infections caused by susceptible anaerobic bacteria. Indicated surgical procedures should be performed in conjunction with FLAGYL therapy. In a mixed aerobic and anaerobic infection, antimicrobials appropriate for the treatment of the aerobic infection should be used in addition to FLAGYL 375 capsules.

INTRA-ABDOMINAL INFECTIONS, including peritonitis, intra-abdominal abscess, and liver abscess, caused by Bacteroides species including the B. fragilis group (B. fragilis, B. distasonis, B. ovatus, B. thetaiotaomicron, B. vulgatus), Clostridium species, Eubacterium species, Peptococcus species, or Peptostreptococcus species.

SKIN AND SKIN STRUCTURE INFECTIONS caused by Bacteroides species including the B. fragilis group, Clostridium species, Peptococcus species, Peptostreptococcus species, or Fusobacterium species.

GYNECOLOGIC INFECTIONS, including endometritis, endomyometritis, tubo-ovarian abscess, and postsurgical vaginal cuff infection, caused by Bacteroides species including the B. fragilis group, Clostridium species, Peptococcus species, Peptostreptococcus species, or Fusobacterium species.

BACTERIAL SEPTICEMIA caused by Bacteroides species including the B. fragilis group or Clostridium species.

BONE AND JOINT INFECTIONS (as adjunctive therapy) caused by Bacteroides species including the B. fragilis group.

CENTRAL NERVOUS SYSTEM (CNS) INFECTIONS, including meningitis and brain abscess, caused by Bacteroides species including the B. fragilis group.

LOWER RESPIRATORY TRACT INFECTIONS, including pneumonia, empyema, and lung abscess, caused by Bacteroides species including the B. fragilis group.

ENDOCARDITIS caused by Bacteroides species including the B. fragilis group.

To reduce the development of drug-resistant bacteria and maintain the effectiveness of FLAGYL 375 capsules and other antibacterial drugs, FLAGYL 375 capsules should be used only to treat or prevent infections that are proven or strongly suspected to be caused by susceptible bacteria. When culture and susceptibility information are available, they should be considered in selecting or modifying antibacterial therapy. In the absence of such data, local epidemiology and susceptibility patterns may contribute to the empiric selection of therapy.

CONTRAINDICATIONS

Hypersensitivity

FLAGYL 375 capsules are contraindicated in patients with a prior history of hypersensitivity to metronidazole or other nitroimidazole derivatives.

In patients with trichomoniasis, FLAGYL 375 capsules are contraindicated during the first trimester of pregnancy (see PRECAUTIONS).

Psychotic Reaction with Disulfiram

Use of oral metronidazole is associated with psychotic reactions in alcoholic patients who were using disulfiram concurrently. Do not administer metronidazole to patients who have taken disulfiram within the last two weeks (see PRECAUTIONS, Drug Interactions).

Interaction with Alcohol

Use of oral metronidazole is associated with a disulfiram-like reaction to alcohol, including abdominal cramps, nausea, vomiting, headaches, and flushing. Discontinue consumption of alcohol or products containing propylene glycol during and for at least three days after therapy with metronidazole (see PRECAUTIONS, Drug Interactions).

Cockayne Syndrome

FLAGYL 375 capsules are contraindicated in patients with Cockayne syndrome. Severe irreversible hepatotoxicity/acute liver failure with fatal outcomes have been reported after initiation of metronidazole in patients with Cockayne syndrome (see ADVERSE REACTIONS).

WARNINGS

Hypersensitivity Reactions

Hypersensitivity reactions including severe cutaneous adverse reactions (SCARs) can be serious and potentially life threatening (see ADVERSE REACTIONS).

Severe cutaneous adverse reactions (SCARs) including toxic epidermal necrolysis (TEN), Stevens-Johnson syndrome (SJS), drug reaction with eosinophilia and systemic symptoms (DRESS), and acute generalized exanthematous pustulosis (AGEP) have been reported with the use of metronidazole. Symptoms can be serious and potentially life threatening. If symptoms or signs of SCARs develop, discontinue FLAGYL capsules immediately and institute appropriate therapy.

Central and Peripheral Nervous System Effects

Encephalopathy and peripheral neuropathy: Cases of encephalopathy and peripheral neuropathy (including optic neuropathy) have been reported with metronidazole.

Encephalopathy has been reported in association with cerebellar toxicity characterized by ataxia, dizziness, and dysarthria. CNS lesions seen on MRI have been described in reports of encephalopathy. CNS symptoms are generally reversible within days to weeks upon discontinuation of metronidazole. CNS lesions seen on MRI have also been described as reversible.

Peripheral neuropathy, mainly of sensory type has been reported and is characterized by numbness or paresthesia of an extremity.

Convulsive seizures have been reported in patients treated with metronidazole.

Aseptic meningitis: Cases of aseptic meningitis have been reported with metronidazole. Symptoms can occur within hours of dose administration and generally resolve after metronidazole therapy is discontinued.

The appearance of abnormal neurologic signs and symptoms demands the prompt evaluation of the benefit/risk ratio of the continuation of therapy (see ADVERSE REACTIONS).

PRECAUTIONS

General

Hepatic Impairment

Patients with hepatic impairment metabolize metronidazole slowly, with resultant accumulation of metronidazole in the plasma. The FLAGYL 375 capsules dosage or the frequency of administration should be reduced in patients with severe (Child-Pugh C) hepatic impairment. For patients with mild to moderate hepatic impairment, no dosage adjustment is needed. Patients with hepatic impairment should be monitored for metronidazole associated adverse events (see CLINICAL PHARMACOLOGY and DOSAGE AND ADMINISTRATION).

Renal Impairment

Patients with end-stage renal disease may excrete metronidazole and metabolites slowly in the urine, resulting in significant accumulation of metronidazole metabolites. Monitoring for metronidazole associated adverse events is recommended (see CLINICAL PHARMACOLOGY).

Fungal Superinfections

Known or previously unrecognized candidiasis may present more prominent symptoms during therapy with FLAGYL 375 capsules and requires treatment with a candidacidal agent.

Use in Patients with Blood Dyscrasias

Metronidazole is a nitroimidazole and should be used with caution in patients with evidence of or history of blood dyscrasia. A mild leucopenia has been observed during its administration; however, no persistent hematologic abnormalities attributable to metronidazole have been observed in clinical studies. Total and differential leukocyte counts are recommended before and after therapy.

Drug-Resistant Bacteria and Parasites

Prescribing FLAGYL 375 capsules in the absence of a proven or strongly suspected bacterial or parasitic infection or a prophylactic indication is unlikely to provide benefit to the patient and increases the risk of the development of drug-resistant bacteria and parasites.

Information for patients

Interaction with Alcohol

Discontinue consumption of alcoholic beverages or products containing propylene glycol while taking FLAGYL 375 capsules and for at least three days afterward because abdominal cramps, nausea, vomiting, headaches, and flushing may occur (see CONTRAINDICATIONS and PRECAUTIONS, Drug Interactions).

Treatment of Bacterial and Parasitic Infections

Patients should be counseled that FLAGYL 375 should only be used to treat bacterial and parasitic infections. They do not treat viral infections (e.g., the common cold). When FLAGYL 375 is prescribed to treat a bacterial infection, patients should be told that although it is common to feel better early in the course of therapy, the medication should be taken exactly as directed. Skipping doses or not completing the full course of therapy may (1) decrease the effectiveness of the immediate treatment and (2) increase the likelihood that bacteria will develop resistance and will not be treatable by FLAGYL 375 in the future.

Severe Cutaneous Adverse Reactions

Advise patients that FLAGYL capsules may increase the risk of serious and sometimes fatal dermatologic reactions, including TEN, SJS, and DRESS. Instruct the patient to be alert for skin rash, blisters, fever or other signs and symptoms of these hypersensitivity reactions. Advise patients to stop FLAGYL capsules immediately if they develop any type of rash and seek medical attention.

Drug interactions

Disulfiram

Psychotic reactions have been reported in alcoholic patients who are using metronidazole and disulfiram concurrently. Metronidazole should not be given to patients who have taken disulfiram within the last 2 weeks (see CONTRAINDICATIONS).

Alcoholic Beverages

Abdominal cramps, nausea, vomiting, headaches, and flushing may occur if alcoholic beverages or products containing propylene glycol are consumed during or following metronidazole therapy (see CONTRAINDICATIONS).

Warfarin and other Oral Anticoagulants

Metronidazole has been reported to potentiate the anticoagulant effect of warfarin and other oral coumarin anticoagulants, resulting in a prolongation of prothrombin time. When FLAGYL 375 capsules is prescribed for patients on this type of anticoagulant therapy prothrombin time and INR should be carefully monitored.

Lithium

In patients stabilized on relatively high doses of lithium, short-term metronidazole therapy has been associated with elevation of serum lithium and, in a few cases, signs of lithium toxicity. Serum lithium and serum creatinine levels should be obtained several days after beginning metronidazole to detect any increase that may precede clinical symptoms of lithium intoxication.

Busulfan

Metronidazole has been reported to increase plasma concentrations of busulfan, which can result in an increased risk for serious busulfan toxicity. Metronidazole should not be administered concomitantly with busulfan unless the benefit outweighs the risk. If no therapeutic alternatives to metronidazole are available, and concomitant administration with busulfan is medically needed, frequent monitoring of busulfan plasma concentration should be performed and the busulfan dose should be adjusted accordingly.

Drugs that Inhibit CYP450 Enzymes

The simultaneous administration of drugs that decrease microsomal liver enzyme activity, such as cimetidine, may prolong the half-life and decrease plasma clearance of metronidazole.

Drugs that Induce CYP450 Enzymes

The simultaneous administration of drugs that induce microsomal liver enzymes, such as phenytoin or phenobarbital, may accelerate the elimination of metronidazole, resulting in reduced plasma levels; impaired clearance of phenytoin has also been reported.

Drugs that Prolong the QT interval

QT prolongation has been reported, particularly when metronidazole was administered with drugs with the potential for prolonging the QT interval.

Drug/Laboratory Test Interactions

Metronidazole may interfere with certain types of determinations of serum chemistry values, such as aspartate aminotransferase (AST, SGOT), alanine aminotransferase (ALT, SGPT), lactate dehydrogenase (LDH), triglycerides, and glucose hexokinase. Values of zero may be observed. All of the assays in which interference has been reported involve enzymatic coupling of the assay to oxidation-reduction of nicotinamide adenine dinucleotide (NAD^+ ⇆ NADH). Interference is due to the similarity in absorbance peaks of NADH (340 nm) and metronidazole (322 nm) at pH 7.

Carcinogenesis, Mutagenesis, Impairment of Fertility

Tumors affecting the liver, lung, mammary and lymphatic tissues have been detected in several studies of metronidazole in rats and mice, but not hamsters.

Pulmonary tumors have been observed in all six reported studies in the mouse, including one study in which the animals were dosed on an intermittent schedule (administration during every fourth week only). Malignant liver tumors were increased in male mice treated at approximately 1500 mg/m^2 (similar to the maximum recommended daily dose, based on body surface area comparisons). Malignant lymphomas and pulmonary neoplasms were also increased with lifetime feeding of the drug to mice. Mammary and hepatic tumors were increased among female rats administered oral metronidazole compared to concurrent controls. Two lifetime tumorigenicity studies in hamsters have been performed and reported to be negative.

Metronidazole has shown mutagenic activity in in vitro assay systems including the Ames test. Studies in mammals in vivo have failed to demonstrate a potential for genetic damage.

Metronidazole failed to produce any adverse effects on fertility or testicular function in male rats at doses up to 400 mg/kg/day (similar to the maximum recommended clinical dose based on body surface area comparisons) for 28 days. However, rats treated at the same dose for 6 weeks or longer were infertile and showed severe degeneration of the seminiferous epithelium in the testes as well as marked decreases in testicular spermatid counts and epididymal sperm counts. Fertility was restored in most rats after an eight week, drug-free recovery period.

Pregnancy:

Teratogenic effects:

There are no adequate and well-controlled studies of FLAGYL 375 capsules in pregnant women. There are published data from case-control studies, cohort studies, and 2‑meta‑analyses that include more than 5000 pregnant women who used metronidazole during pregnancy. Many studies included first trimester exposures. One study showed an increased risk of cleft lip, with or without cleft palate, in infants exposed to metronidazole in-utero; however, these finding were not confirmed. In addition, more than ten randomized placebo-controlled clinical trials enrolled more than 5000 pregnant women to assess the use of antibiotic treatment (including metronidazole) for bacterial vaginosis on the incidence of preterm delivery. Most studies did not show an increased risk for congenital abnormalities or other adverse fetal outcomes following metronidazole exposure during pregnancy. Three studies conducted to assess the risk of infant cancer following metronidazole exposure during pregnancy did not show an increased risk; however, the ability of these studies to detect such a signal was limited.

Metronidazole crosses the placental barrier and its effects on the human fetal organogenesis are not known. Reproduction studies have been performed in rats, rabbits, and mice at doses similar to the maximum recommended human dose based on body surface area comparisons. There was no evidence of harm to the fetus due to metronidazole.

Nursing mothers

Metronidazole is present in human milk at concentrations similar to maternal serum levels, and infant serum levels can be close to or comparable to infant therapeutic levels. There are no data on the effects of metronidazole on milk production. Animal studies have shown the potential for tumorigenicity after oral metronidazole was administered chronically to rats and mice (see PRECAUTIONS, Carcinogenesis, Mutagenesis, Impairment of Fertility). This drug is not intended to be administered chronically; therefore, the clinical relevance of the findings of the animal studies is unclear. The developmental and health benefits of breastfeeding should be considered along with the mother’s clinical need for FLAGYL and any potential adverse effects on the breastfed infant from FLAGYL or from the underlying maternal condition. Alternatively, a nursing mother may choose to pump and discard human milk for the duration of FLAGYL therapy, and for 48 hours after the last dose and feed her infant stored human milk or formula.

Geriatric use

In geriatric patients, monitoring for metronidazole associated adverse events is recommended (see CLINICAL PHARMACOLOGY and PRECAUTIONS). Decreased liver function in geriatric patients can result in increased concentrations of metronidazole that may necessitate adjustment of metronidazole dosage (see DOSAGE AND ADMINISTRATION).

Pediatric use

Safety and effectiveness in pediatric patients have not been established, except in the treatment of amebiasis.

ADVERSE REACTIONS

The following reactions have been reported during treatment with metronidazole:

Central Nervous System: The most serious adverse reactions reported in patients treated with metronidazole have been convulsive seizures, encephalopathy, aseptic meningitis, optic and peripheral neuropathy, the latter characterized mainly by numbness or paresthesia of an extremity. Since persistent peripheral neuropathy has been reported in some patients receiving prolonged administration of metronidazole, patients should be specifically warned about these reactions and should be told to stop the drug and report immediately to their physicians if any neurologic symptoms occur. In addition, patients have reported headache, syncope, dizziness, vertigo, incoordination, ataxia, tinnitus, hearing impairment, hearing loss, confusion, dysarthria, irritability, depression, weakness, and insomnia (see WARNINGS).

Gastrointestinal: The most common adverse reactions reported have been referable to the gastrointestinal tract, particularly nausea, sometimes accompanied by headache, anorexia, and occasionally vomiting; diarrhea; epigastric distress; abdominal cramping; and constipation.

Mouth: A sharp, unpleasant metallic taste is not unusual. Furry tongue, glossitis, and stomatitis have occurred; these may be associated with a sudden overgrowth of Candida which may occur during therapy.

Dermatologic: Dermatitis bullous, fixed drug eruption, erythematous rash and pruritus.

Hematopoietic: Reversible neutropenia (leukopenia); rarely, reversible thrombocytopenia.

Cardiovascular: QT prolongation has been reported, particularly when metronidazole was administered with drugs with the potential for prolonging the QT interval. Flattening of the T-wave may be seen in electrocardiographic tracings.

Hypersensitivity: Toxic epidermal necrolysis (TEN), Stevens-Johnson Syndrome (SJS), drug reaction with eosinophilia and systemic symptoms (DRESS), acute generalized exanthematous pustulosis (AGEP) (see WARNINGS), urticaria, erythematous rash, flushing, nasal congestion, dryness of the mouth (or vagina or vulva), and fever.

Renal: Dysuria, cystitis, polyuria, incontinence, and a sense of pelvic pressure. Instances of darkened urine have been reported by approximately one patient in 100,000. Although the pigment which is probably responsible for this phenomenon has not been positively identified, it is almost certainly a metabolite of metronidazole and seems to have no clinical significance.

Hepatic: Cases of severe irreversible hepatotoxicity/acute liver failure, including cases with fatal outcomes with very rapid onset after initiation of systemic use of metronidazole, have been reported in patients with Cockayne syndrome (latency from drug start to signs of liver failure as short as 2 days) (see CONTRAINDICATIONS).

Other: Proliferation of Candida in the vagina, dyspareunia, decrease of libido, proctitis, and fleeting joint pains sometimes resembling "serum sickness." Rare cases of pancreatitis, which generally abated on withdrawal of the drug, have been reported.

Patients with Crohn's disease are known to have an increased incidence of gastrointestinal and certain extraintestinal cancers. There have been some reports in the medical literature of breast and colon cancer in Crohn's disease patients who have been treated with metronidazole at high doses for extended periods of time. A cause and effect relationship has not been established. Crohn's disease is not an approved indication for FLAGYL 375 capsules.

OVERDOSAGE

Single oral doses of metronidazole, up to 15 g, have been reported in suicide attempts and accidental overdoses. Symptoms reported include nausea, vomiting, and ataxia.

Oral metronidazole has been studied as a radiation sensitizer in the treatment of malignant tumors. Neurotoxic effects, including seizures and peripheral neuropathy, have been reported after 5 to 7 days of doses of 6 to 10.4 g every other day.

Treatment of Overdosage:

There is no specific antidote for metronidazole overdose; therefore, management of the patient should consist of symptomatic and supportive therapy.

DOSAGE AND ADMINISTRATION

Trichomoniasis

In the Female: Seven-day course of treatment (375 mg two times daily for seven consecutive days).

A seven-day course of treatment may minimize reinfection by protecting the patient long enough for the sexual contacts to obtain treatment. Pregnant patients should not be treated during the first trimester (see CONTRAINDICATIONS and PRECAUTIONS).

When repeat courses of the drug are required, it is recommended that an interval of four to six weeks elapse between courses and that the presence of the trichomonad be reconfirmed by appropriate laboratory measures. Total and differential leukocyte counts should be made before and after re-treatment.

In the Male: Treatment should be individualized as it is for the female.

Amebiasis:

Adults:

For acute intestinal amebiasis (acute amebic dysentery): 750 mg orally three times daily for 5 to 10 days.

For amebic liver abscess: 750 mg orally three times daily for 5 to 10 days.

Pediatric patients: 35 to 50 mg/kg/24 hours, divided into three doses, orally for 10 days.

Anaerobic Bacterial Infections

In the treatment of most serious anaerobic infections, intravenous metronidazole is usually administered initially.

The usual adult oral dosage is 7.5 mg/kg every 6 hours (approximately 500 mg for a 70 kg adult). A maximum of 4 g should not be exceeded during a 24-hour period.

The usual duration of therapy is 7 to 10 days; however, infections of the bone and joint, lower respiratory tract, and endocardium may require longer treatment.

Dosage Adjustments

Patients with Severe Hepatic impairment

For amebiasis patients with severe (Child-Pugh C) hepatic impairment, pharmacokinetic modeling and simulation indicate that the FLAGYL 375 capsules dose should be reduced by 50%. Therefore, the dosage regimen of FLAGYL 375 capsules in Child Pugh C patients with amebiasis is 375 mg q8h for 5 to 10 days (see CLINICAL PHARMACOLOGY and PRECAUTIONS).

For trichomoniasis patients with severe (Child-Pugh C) hepatic impairment, pharmacokinetic modeling and simulation indicate that the frequency of metronidazole administration should be reduced from every 12 hours to every 24 hours. Therefore, the dosage regiment of FLAGYL 375 capsules in Child Pugh C patients with trichomoniasis is 375 mg q24h for 7 days (see CLINICAL PHARMACOLOGY and PRECAUTIONS).

Patients Undergoing Hemodialysis

Hemodialysis removes significant amounts of metronidazole and its metabolites from systemic circulation. The clearance of metronidazole will depend on the type of dialysis membrane used, the duration of the dialysis session, and other factors. If the administration of metronidazole cannot be separated from a hemodialysis session, supplementation of metronidazole dosage following the hemodialysis session should be considered, depending on the patient's clinical situation (see CLINICAL PHARMACOLOGY).

HOW SUPPLIED

FLAGYL 375 capsules have an iron gray opaque body imprinted with 375 mg and a light green opaque cap imprinted with FLAGYL, supplied as:

NDC Number Size
0025-1942-34 Carton of 100 unit dose

Storage and Stability:

Store at controlled room temperature 15–25°C (59–77°F). Dispense in a well-closed container with a child-resistant closure.

This product’s labeling may have been updated. For the most recent prescribing information, please visit www.pfizer.com.

LAB-0163-20.0
Revised: 07/2025

PRINCIPAL DISPLAY PANEL - 375 mg Capsule Bottle Label

Pfizer
NDC 0025-1942-50

Flagyl® 375
(metronidazole)
capsules

375 mg

50 Capsules
Rx only